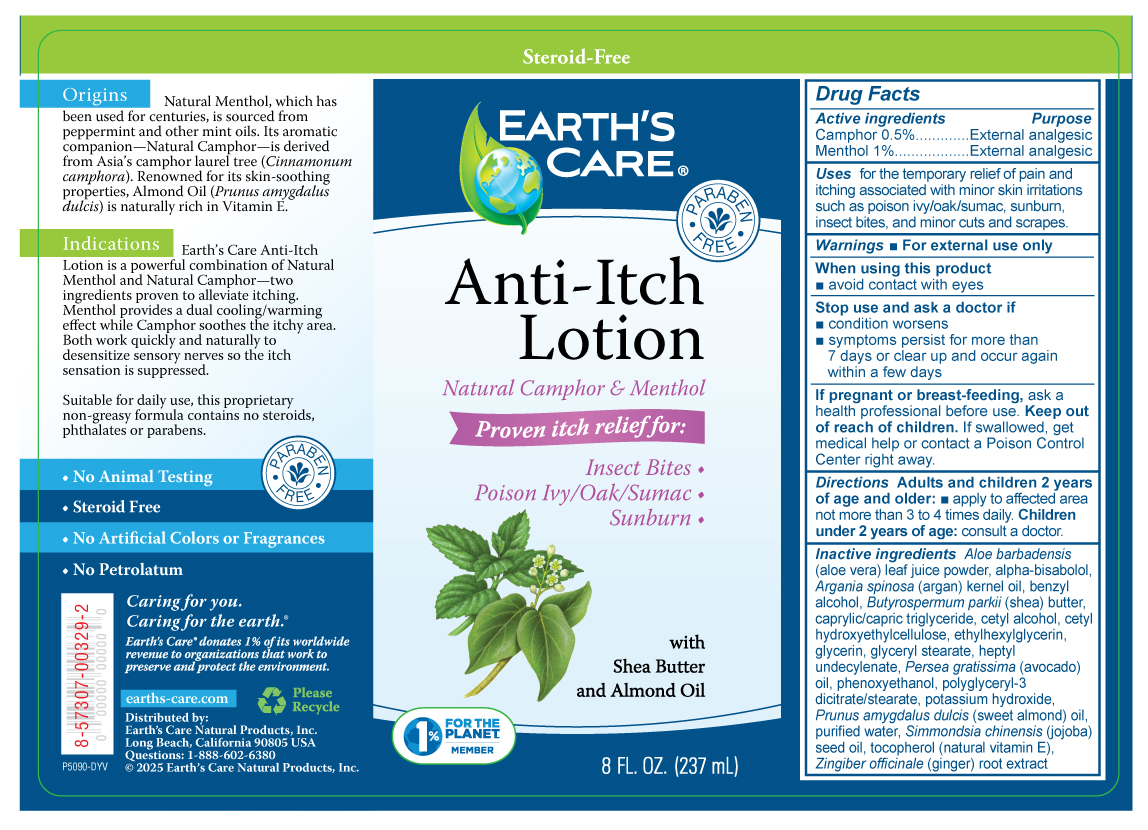 DRUG LABEL: Earths Care Anti-Itch
NDC: 24286-1576 | Form: LOTION
Manufacturer: DLC Laboratories, Inc.
Category: otc | Type: HUMAN OTC DRUG LABEL
Date: 20250613

ACTIVE INGREDIENTS: CAMPHOR (NATURAL) 0.5 g/100 mL; MENTHOL, UNSPECIFIED FORM 1 g/100 mL
INACTIVE INGREDIENTS: BENZYL ALCOHOL; POLYGLYCERYL-3 DICITRATE/STEARATE; CAPRYLIC/CAPRIC TRIGLYCERIDE; GLYCERYL MONOSTEARATE; CETYL ALCOHOL; ALMOND OIL; HEPTYL UNDECYLENATE; JOJOBA OIL; AVOCADO OIL; .ALPHA.-BISABOLOL, (+/-)-; ARGAN OIL; PHENOXYETHANOL; ETHYLHEXYLGLYCERIN; TOCOPHEROL; GINGER; ALOE VERA LEAF; CETYL HYDROXYETHYLCELLULOSE (350000 MW); POTASSIUM HYDROXIDE; GLYCERIN; SHEA BUTTER; WATER

Earth's Care® Anti-Itch

Drug Facts

ACTIVE INGREDIENT

Camphor 0.5% external analgesic

Menthol 1% external analgesic

Active ingredients | Purpose
Camphor 0.5% | External analgesic
Menthol 1% | External analgesic

Uses

for the temporary relief of pain and itching associated with minor skin irritations such as poison ivy/oak/sumac, sunburn, insect bites, and minor cuts and scrapes.

Warnings

- For external use only

When using this product

- avoid contact with eyes

Stop use and ask a doctor if

- condition worsens
- symptoms persist for more than 7 days or clear up and occur again within a few days

PREGNANCY OR BREAST FEEDING

If pregnant or breast-feeding, ask a health professional before use.

Keep out of reach of children. If swallowed, get medical help or contact a Poison Control Center right away.

When using this product

avoid contact with eyes

Stop use and ask a doctor if

condition worsens

symptoms persis for more than 7 days or clear up and occure again within a few days

If pregnant or breast-feeding

ask a health professional before use.

Keep out of reach of children

If swallowed, get medical help or contact a Poison Control Center right away.

Directions

Adults and children 2 years of age and older:

- apply to affected area not more than 3 to 4 times daily.

Children under 2 years of age: consult a doctor.

Inactive ingredients

Aloe barbadensis (aloe vera) leaf juice powder, alpha-bisabolol, Argania spinosa (argan) kernel oil, benzyl alcohol, Butyrospermum parkii (shea) butter, caprylic/capric triglyceride, cetyl alcohol, cetyl hydroxyethylcellulose, ethylhexylglycerin, glycerin, glyceryl stearate, heptyl undecylenate, Persea gratissima (avocado) oil, phenoxyethanol, polyglyceryl-3 dicitrate/stearate, potassium hydroxide, Prunus amygdalus dulcis (sweet almond) oil, purified water, Simmondsia chinensis (jojoba) seed oil, tocopherol (natural vitamin E), Zingiber officinale (ginger) root extract.

Questions

1-888-602-6380

earths-care.com

Distributed by Earth's Care Natural Products, Inc.

Long Beach, California 90805, USA

PRINCIPAL DISPLAY PANEL - 237 mL Bottle Label

Steroid-Free

EARTH'S
CARE®
• PARABEN

FREE•

Anti-Itch

Lotion

Natural Camphor & Menthol

Proven itch relief for:

Insect Bites ♦
Poison Ivy/Oak/sumac ♦
Sunburn ♦

with
Shea Butter
and Almond Oil

1%
FOR THE
PLANETSM
MEMBER

8 FL. OZ. (237 mL)